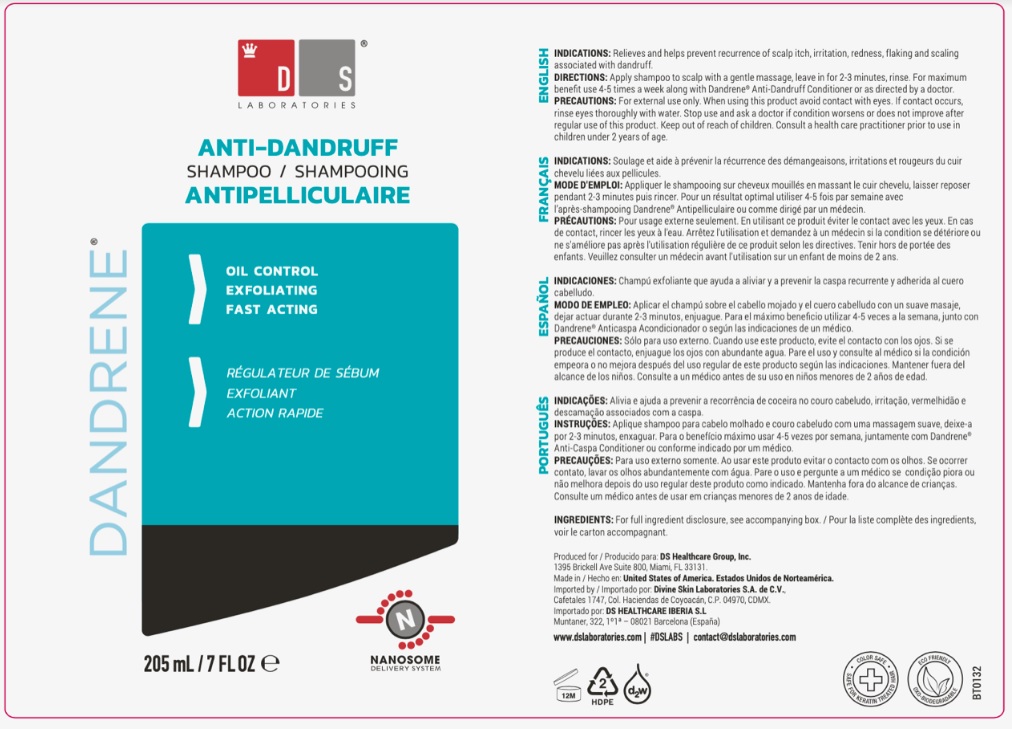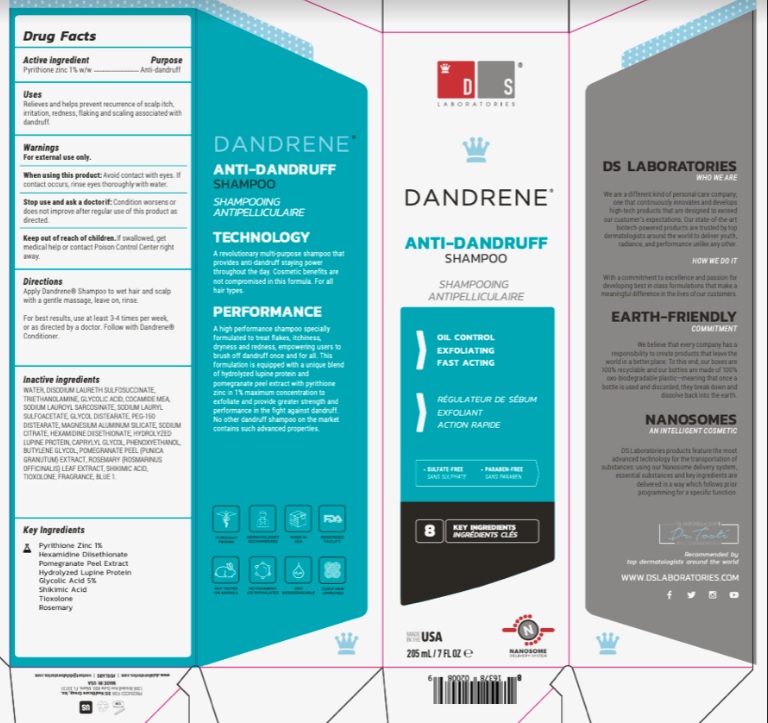 DRUG LABEL: Divine Dandrene 1%
NDC: 69188-100 | Form: SHAMPOO
Manufacturer: DS Healthcare Group, Inc.
Category: otc | Type: HUMAN OTC DRUG LABEL
Date: 20251111

ACTIVE INGREDIENTS: PYRITHIONE ZINC 1 g/100 mL
INACTIVE INGREDIENTS: WATER; DISODIUM LAURETH SULFOSUCCINATE; TROLAMINE; GLYCOLIC ACID; COCO MONOETHANOLAMIDE; SODIUM LAUROYL SARCOSINATE; SODIUM LAURYL SULFOACETATE; MAGNESIUM ALUMINUM SILICATE; GLYCOL DISTEARATE; PEG-150 DISTEARATE; SODIUM CITRATE; HEXAMIDINE DIISETHIONATE; SURINAMINE; CAPRYLYL GLYCOL; PHENOXYETHANOL; BUTYLENE GLYCOL; PUNICA GRANATUM FLOWER; ROSEMARY; SHIKIMIC ACID; TIOXOLONE; FD&C BLUE NO. 1

Active ingredient

Zinc Pyrithione 1%

Purpose

Anti-dandruff

Uses

Relieves and helps prevent recurrence of scalp itch, irritation, redness, flaking and scaling associated with dandruff

Warnings

For external use only.

When using this Product: Avoid contact with eyes, If contact occurs, rinse eyes thoroughly with water

Stop use and ask a doctor if Condition worsens or does not improve after regular use of this product as directed

Keep out of reach of children. If swallowed, get medical help or contact Poison Control Center right away

Directions

Apply shampoo to wet hair and scalp with gentle massage, leave in for 2-3 minutes, rinse

For best results use atleast 2 times per week or as direacted by a doctor

For maximum benefits use 4-5 times a week along with Dandrene anti-dandruff conditioner

Inactive ingredients

Water, Disodium Laureth Sulfosuccinate, Triethanolamine, Glycolic Acid, Cocamide MEA, Sodium Lauroyl Sarcosinate, Sodium Lauryl Suloacetate, Glycol Distearate, PEG-150 Distearate, Magnesium Aluminum Silicate, Sodium Citrate, Hexamidine Diisethionate, Hydrolyzed Lupine
Protein, Caprylyl Glycol, Phenoxyethanol, Butylene Glycol, Punica Granatum Extract, Rosmarinus Officinalis Leaf Extract, Shikimic Acid, Tioxolone, Blue 1